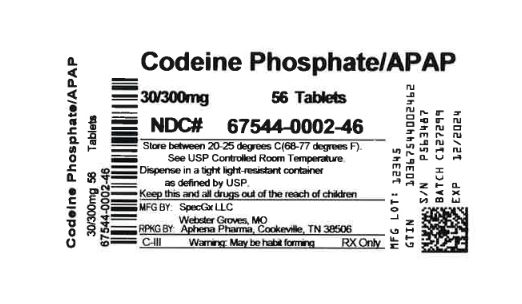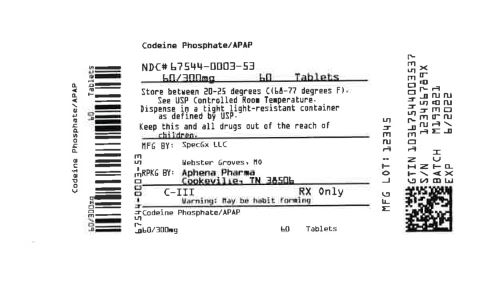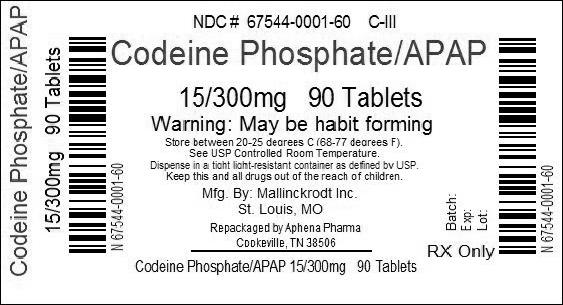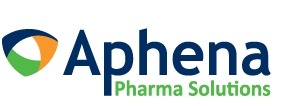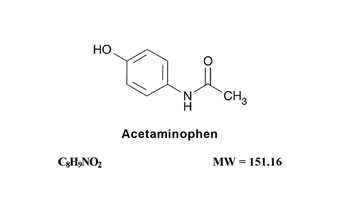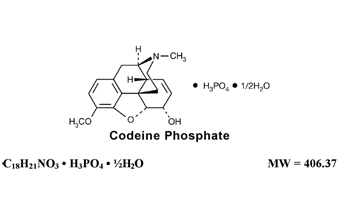 DRUG LABEL: ACETAMINOPHEN AND CODEINE PHOSPHATE
NDC: 67544-001 | Form: TABLET
Manufacturer: Aphena Pharma Solutions - Tennessee, LLC
Category: prescription | Type: HUMAN PRESCRIPTION DRUG LABEL
Date: 20250108
DEA Schedule: CIII

ACTIVE INGREDIENTS: ACETAMINOPHEN 300 mg/1 1; CODEINE PHOSPHATE 15 mg/1 1
INACTIVE INGREDIENTS: CROSPOVIDONE; MAGNESIUM STEARATE; CELLULOSE, MICROCRYSTALLINE; POVIDONE, UNSPECIFIED; STARCH, CORN; STEARIC ACID

ACETAMINOPHEN AND CODEINE PHOSPHATE TABLETS USP
(300 mg/15 mg, 300 mg/30 mg, 300 mg/60 mg)
CIII
Rx only

WARNING: Hepatotoxicity

Acetaminophen has been associated with cases of acute liver failure, at times resulting in liver transplant and death. Most of the cases of liver injury are associated with the use of acetaminophen at doses that exceed 4000 milligrams per day, and often involve more than one acetaminophen-containing product (see WARNINGS).

WARNING: Death Related to Ultra-Rapid Metabolism of Codeine to Morphine

Respiratory depression and death have occurred in children who received codeine following tonsillectomy and/or adenoidectomy and had evidence of being ultra-rapid metabolizers of codeine due to a CYP2D6 polymorphism.

DESCRIPTION

Acetaminophen and codeine phosphate is supplied in tablet form for oral administration.

Acetaminophen, 4'-hydroxyacetanilide, a slightly bitter, white, odorless, crystalline powder, is a non-opiate, non-salicylate analgesic and antipyretic. It has the following structural formula:

Codeine phosphate, 7,8-didehydro-4,5α-epoxy-3-methoxy-17-methylmorphinan-6α-ol phosphate (1:1) (salt) hemihydrate, a white crystalline powder, is a narcotic analgesic and antitussive. It has the following structural formula:

Each Acetaminophen and Codeine Phosphate Tablet USP (300 mg/15 mg) contains:

Acetaminophen USP . . . . . . . . . . . . . 300 mg

Codeine Phosphate USP . . . . . . . . . . . . . 15 mg
(Warning: May be habit forming)

Each Acetaminophen and Codeine Phosphate Tablet USP (300 mg/30 mg) contains:

Acetaminophen USP . . . . . . . . . . . . . 300 mg

Codeine Phosphate USP . . . . . . . . . . . . . 30 mg
(Warning: May be habit forming)

Each Acetaminophen and Codeine Phosphate Tablet USP (300 mg/60 mg) contains:

Acetaminophen USP . . . . . . . . . . . . . 300 mg

Codeine Phosphate USP . . . . . . . . . . . . . 60 mg
(Warning: May be habit forming)

In addition, each Acetaminophen and Codeine Phosphate Tablet USP contains the following inactive ingredients: crospovidone, magnesium stearate, microcrystalline cellulose, povidone, pregelatinized starch, stearic acid.

CLINICAL PHARMACOLOGY

This product combines the analgesic effects of a centrally acting analgesic, codeine, with a peripherally acting analgesic, acetaminophen.

Pharmacokinetics

The behavior of the individual components is described below.

Codeine – Codeine is rapidly absorbed from the gastrointestinal tract. It is rapidly distributed from the intravascular spaces to the various body tissues, with preferential uptake by parenchymatous organs such as the liver, spleen and kidney. Codeine crosses the blood-brain barrier, and is found in fetal tissue and breast milk. The plasma concentration does not correlate with brain concentration or relief of pain; however, codeine is not bound to plasma proteins and does not accumulate in body tissues.

The plasma half-life is about 2.9 hours. The elimination of codeine is primarily via the kidneys, and about 90% of an oral dose is excreted by the kidneys within 24 hours of dosing. The urinary secretion products consist of free and glucuronide conjugated codeine (about 70%), free and conjugated norcodeine (about 10%), free and conjugated morphine (about 10%), normorphine (4%), and hydrocodone (1%). The remainder of the dose is excreted in the feces.

At therapeutic doses, the analgesic effect reaches a peak within 2 hours and persists between 4 and 6 hours.

Acetaminophen – Acetaminophen is rapidly absorbed from the gastrointestinal tract and is distributed throughout most body tissues. The plasma half-life is 1.25 to 3 hours, but may be increased by liver damage and following overdosage. Elimination of acetaminophen is principally by liver metabolism (conjugation) and subsequent renal excretion of metabolites. Approximately 85% of an oral dose appears in the urine within
24 hours of administration, most as the glucuronide conjugate, with small amounts of other conjugates and unchanged drug.

INDICATIONS AND USAGE

Acetaminophen and codeine phosphate tablets are indicated for the relief of mild to moderately severe pain.

CONTRAINDICATIONS

Codeine-containing products are contraindicated for postoperative pain management in children who have undergone tonsillectomy and/or adenoidectomy.

This product should not be administered to patients who have previously exhibited hypersensitivity to codeine or acetaminophen.

WARNINGS

Hepatotoxicity

Acetaminophen has been associated with cases of acute liver failure, at times resulting in liver transplant and death. Most of the cases of liver injury are associated with the use of acetaminophen at doses that exceed 4000 milligrams per day, and often involve more than one acetaminophen-containing product. The excessive intake of acetaminophen may be intentional to cause self-harm or unintentional as patients attempt to obtain more pain relief or unknowingly take other acetaminophen-containing products.

The risk of acute liver failure is higher in individuals with underlying liver disease and in individuals who ingest alcohol while taking acetaminophen.

Instruct patients to look for acetaminophen or APAP on package labels and not to use more than one product that contains acetaminophen. Instruct patients to seek medical attention immediately upon ingestion of more than 4000 milligrams of acetaminophen per day, even if they feel well.

Serious Skin Reactions

Rarely, acetaminophen may cause serious skin reactions such as acute generalized exanthematous pustulosis (AGEP), Stevens-Johnson Syndrome (SJS), and toxic epidermal necrolysis (TEN), which can be fatal. Patients should be informed about the signs of serious skin reactions, and use of the drug should be discontinued at the first appearance of skin rash or any other sign of hypersensitivity.

Death Related to Ultra-Rapid Metabolism of Codeine to Morphine

Respiratory depression and death have occurred in children who received codeine in the postoperative period following tonsillectomy and/or adenoidectomy and had evidence of being ultra-rapid metabolizers of codeine (i.e., multiple copies of the gene for cytochrome P450 isoenzyme 2D6 or high morphine concentrations). Deaths have also occurred in nursing infants who were exposed to high levels of morphine in breast milk because their mothers were ultra-rapid metabolizers of codeine (see PRECAUTIONS, Nursing Mothers).

Some individuals may be ultra-rapid metabolizers because of a specific CYP2D6 genotype (gene duplications denoted as *1/*1xN or *1/*2xN). The prevalence of this CYP2D6 phenotype varies widely and has been estimated at 0.5 to 1% in Chinese and Japanese, 0.5 to 1% in Hispanics, 1 to 10% in Caucasians, 3% in African Americans, and 16 to 28% in North Africans, Ethiopians, and Arabs. Data are not available for other ethnic groups. These individuals convert codeine into its active metabolite, morphine, more rapidly and completely than other people. This rapid conversion results in higher than expected serum morphine levels. Even at labeled dosage regimens, individuals who are ultra-rapid metabolizers may have life-threatening or fatal respiratory depression or experience signs of overdose (such as extreme sleepiness, confusion, or shallow breathing) (see OVERDOSAGE).

Children with obstructive sleep apnea who are treated with codeine for post-tonsillectomy and/or adenoidectomy pain may be particularly sensitive to the respiratory depressant effects of codeine that has been rapidly metabolized to morphine. Codeine-containing products are contraindicated for post-operative pain management in all pediatric patients undergoing tonsillectomy and/or adenoidectomy (see CONTRAINDICATIONS).

When prescribing codeine-containing products, healthcare providers should choose the lowest effective dose for the shortest period of time and inform patients and caregivers about these risks and the signs of morphine overdose (see OVERDOSAGE).

Hypersensitivity/Anaphylaxis

There have been post-marketing reports of hypersensitivity and anaphylaxis associated with the use of acetaminophen. Clinical signs included swelling of the face, mouth, and throat, respiratory distress, urticaria, rash, pruritus, and vomiting. There were infrequent reports of life-threatening anaphylaxis requiring emergency medical attention. Instruct patients to discontinue acetaminophen and codeine phosphate tablets USP immediately and seek medical care if they experience these symptoms. Do not prescribe acetaminophen and codeine phosphate tablets USP for patients with acetaminophen allergy.

Head Injuries

In the presence of head injury or other intracranial lesions, the respiratory-depressant effects of codeine and other narcotics may be markedly enhanced, as well as their capacity for elevating cerebrospinal fluid pressure. Narcotics also produce other CNS-depressant effects, such as drowsiness, that may further obscure the clinical course of the patients with head injuries.

Acute Abdominal Conditions

Codeine or other narcotics may obscure signs on which to judge the diagnosis or clinical course of patients with acute abdominal conditions.

Abuse Potential

Codeine is habit-forming and potentially abusable. Consequently, the extended use of this product is not recommended.

PRECAUTIONS

General

Acetaminophen and codeine phosphate tablets should be prescribed with caution in certain special-risk patients, such as the elderly or debilitated, and those with severe impairment of renal or hepatic function, head injuries, elevated intracranial pressure, acute abdominal conditions, hypothyroidism, urethral stricture, Addison’s disease, or prostatic hypertrophy.

Information for Patients/Caregivers

- Do not take acetaminophen and codeine phosphate tablets USP if you are allergic to any of its ingredients.
- If you develop signs of allergy such as a rash or difficulty breathing, stop taking acetaminophen and codeine phosphate tablets USP and contact your healthcare provider immediately.
- Do not take more than 4000 milligrams of acetaminophen per day. Call your healthcare provider if you took more than the recommended dose.
- Codeine may impair the mental and/or physical abilities required for the performance of potentially hazardous tasks such as driving a car or operating machinery. Avoid such tasks while taking this product.
- Alcohol and other CNS depressants may produce an additive CNS depression when taken with this combination product. Avoid drinking alcohol or taking other CNS depressants when you are taking acetaminophen and codeine phosphate tablets USP.
- Codeine may be habit-forming. Take this drug only for as long as it is prescribed, in the amounts prescribed, and no more frequently than prescribed.
- Advise patients that some people have a genetic variation that results in codeine changing into morphine more rapidly and completely than other people. Most people are unaware of whether they are an ultra-rapid codeine metabolizer or not. These higher-than-normal levels of morphine in the blood may lead to life-threatening or fatal respiratory depression or signs of overdose such as extreme sleepiness, confusion, or shallow breathing. Children with this genetic variation who were prescribed codeine after tonsillectomy and/or adenoidectomy for obstructive sleep apnea may be at greatest risk based on reports of several deaths in this population due to respiratory depression. Codeine-containing products are contraindicated in all children who undergo tonsillectomy and/or adenoidectomy. Advise caregivers of children receiving codeine-containing products for other reasons to monitor for signs of respiratory depression.
- Nursing mothers taking codeine can also have higher morphine levels in their breast milk if they are ultra-rapid metabolizers. These higher levels of morphine in breast milk may lead to life-threatening or fatal side effects in nursing babies. If you are a nursing mother, watch for signs of morphine toxicity in your infant, including increased sleepiness (more than usual), difficulty breastfeeding, breathing difficulties, or limpness. Talk to your baby’s doctor immediately if you notice these signs. If you cannot reach the doctor right away, take your baby to an emergency room or call 911 (or local emergency services).

Laboratory Tests

In patients with severe hepatic or renal disease, effects of therapy should be monitored with serial liver and/or renal function tests.

Drug Interactions

This drug may enhance the effects of other narcotic analgesics, alcohol, general anesthetics, tranquilizers such as chlordiazepoxide, sedative-hypnotics, or other CNS depressants, causing increased CNS depression.

Drug/Laboratory Test Interactions

Codeine may increase serum amylase levels.

Acetaminophen may produce false-positive test results for urinary 5-hydroxyindoleacetic acid.

Carcinogenesis, Mutagenesis, Impairment of Fertility

No adequate studies have been conducted in animals to determine whether acetaminophen and codeine have a potential for carcinogenesis or mutagenesis. No adequate studies have been conducted in animals to determine whether acetaminophen has a potential for impairment of fertility.

Acetaminophen and codeine have been found to have no mutagenic potential using the Ames Salmonella-Microsomal Activation test, the Basc test on Drosophila germ cells, and the Micronucleus test on mouse bone marrow.

Pregnancy

Teratogenic Effects. Pregnancy Category C

Codeine – A study in rats and rabbits reported no teratogenic effect of codeine administered during the period of organogenesis in doses ranging from 5 to 120 mg/kg. In the rat, doses at the 120 mg/kg level, in the toxic range for the adult animal, were associated with an increase in embryo resorption at the time of implantation. In another study a single 100 mg/kg dose of codeine administered to pregnant mice reportedly resulted in delayed ossification in the offspring.

There are no adequate and well-controlled studies in pregnant women. Acetaminophen and codeine phosphate should be used during pregnancy only if the potential benefit justifies the potential risk to the fetus.

Nonteratogenic Effects

Dependence has been reported in newborns whose mothers took opiates regularly during pregnancy. Withdrawal signs include irritability, excessive crying, tremors, hyperreflexia, fever, vomiting, and diarrhea. These signs usually appear during the first few days of life.

Labor and Delivery

Narcotic analgesics cross the placental barrier. The closer to delivery and the larger the dose used, the greater the possibility of respiratory depression in the newborn. Narcotic analgesics should be avoided during labor if delivery of a premature infant is anticipated. If the mother has received narcotic analgesics during labor, newborn infants should be observed closely for signs of respiratory depression. Resuscitation may be required (see OVERDOSAGE). The effect of codeine, if any, on the later growth, development, and functional maturation of the child is unknown.

Nursing Mothers

Acetaminophen is excreted in breast milk in small amounts, but the significance of its effect on nursing infants is not known. Because of the potential for serious adverse reactions in nursing infants from acetaminophen, a decision should be made whether to discontinue nursing or discontinue the drug, taking into account the importance of the drug to the mother.

Codeine is secreted into human milk. In women with normal codeine metabolism
(normal CYP2D6 activity), the amount of codeine secreted into human milk is low and dose-dependent. Despite the common use of codeine products to manage postpartum pain, reports of adverse events in infants are rare. However, some women are ultra-rapid metabolizers of codeine. These women achieve higher-than-expected serum levels of codeine’s active metabolite, morphine, leading to higher-than-expected levels of morphine in breast milk and potentially dangerously high serum morphine levels in their breastfed infants. Therefore, maternal use of codeine can potentially lead to serious adverse reactions, including death, in nursing infants.

The risk of infant exposure to codeine and morphine through breast milk should be weighed against the benefits of breastfeeding for both the mother and baby. Caution should be exercised when codeine is administered to a nursing woman. If a codeine-containing product is selected, the lowest dose should be prescribed for the shortest period of time to achieve the desired clinical effect. Mothers using codeine should be informed about when to seek immediate medical care and how to identify the signs and symptoms of neonatal toxicity, such as drowsiness or sedation, difficulty breastfeeding, breathing difficulties, and decreased tone, in their baby. Nursing mothers who are ultra-rapid metabolizers may also experience overdose symptoms such as extreme sleepiness, confusion or shallow breathing. Prescribers should closely monitor mother-infant pairs and notify treating pediatricians about the use of codeine during breastfeeding (see WARNINGS, Death Related to Ultra-Rapid Metabolism of Codeine to Morphine).

Pediatric Use

Respiratory depression and death have occurred in children with obstructive sleep apnea who received codeine in the postoperative period following tonsillectomy and/or adenoidectomy and had evidence of being ultra-rapid metabolizers of codeine (i.e., multiple copies of the gene for cytochrome P450 isoenzyme CYP2D6 or high morphine concentrations). These children may be particularly sensitive to the respiratory depressant effects of codeine that has been rapidly metabolized to morphine. Codeine-containing products are contraindicated for postoperative pain management in all pediatric patients undergoing tonsillectomy and/or adenoidectomy (see CONTRAINDICATIONS and WARNINGS).

ADVERSE REACTIONS

The most frequently observed adverse reactions include drowsiness, lightheadedness, dizziness, sedation, shortness of breath, nausea and vomiting. These effects seem to be more prominent in ambulatory than in non-ambulatory patients, and some of these adverse reactions may be alleviated if the patient lies down. Other adverse reactions include allergic reactions, euphoria, dysphoria, constipation, abdominal pain, pruritus, rash, thrombocytopenia, and agranulocytosis.

At higher doses, codeine has most of the disadvantages of morphine including respiratory depression.

DRUG ABUSE AND DEPENDENCE

Controlled Substance

Acetaminophen and codeine phosphate tablets are classified as a Schedule III controlled substance.

Abuse and Dependence

Codeine can produce drug dependence of the morphine type and, therefore, has the potential for being abused. Psychological dependence, physical dependence, and tolerance may develop upon repeated administration and it should be prescribed and administered with the same degree of caution appropriate to the use of other oral narcotic medications.

OVERDOSAGE

Following an acute overdosage, toxicity may result from codeine or acetaminophen.

Signs and Symptoms

Toxicity from codeine poisoning includes the opioid triad of pinpoint pupils, depression of respiration, and loss of consciousness. Convulsions may occur.

In acetaminophen overdosage, dose-dependent, potentially fatal hepatic necrosis is the most serious adverse effect. Renal tubular necrosis, hypoglycemic coma and coagulation defects may also occur. Early symptoms following a potentially hepatotoxic overdose may include nausea, vomiting, diaphoresis and general malaise. Clinical and laboratory evidence of hepatic toxicity may not be apparent until 48 to 72 hours post-ingestion.

Treatment

A single or multiple drug overdose with acetaminophen and codeine is a potentially lethal polydrug overdose, and consultation with a regional poison control center is recommended. Immediate treatment includes support of cardiorespiratory function and measures to reduce drug absorption.

Oxygen, intravenous fluids, vasopressors, and other supportive measures should be employed as indicated. Assisted or controlled ventilation should also be considered. For respiratory depression due to overdosage or unusual sensitivity to codeine, parenteral naloxone is a specific and effective antagonist.

Gastric decontamination with activated charcoal should be administered just prior to
N-acetylcysteine (NAC) to decrease systemic absorption if acetaminophen ingestion is known or suspected to have occurred within a few hours of presentation. Serum acetaminophen levels should be obtained immediately if the patient presents 4 or more hours after ingestion to assess potential risk of hepatotoxicity; acetaminophen levels drawn less than 4 hours post-ingestion may be misleading. To obtain the best possible outcome, NAC should be administered as soon as possible where impending or evolving liver injury is suspected. Intravenous NAC may be administered when circumstances preclude oral administration.

Vigorous supportive therapy is required in severe intoxication. Procedures to limit the continuing absorption of the drug must be readily performed since the hepatic injury is dose-dependent and occurs early in the course of intoxication.

DOSAGE AND ADMINISTRATION

Dosage should be adjusted according to severity of pain and response of the patient.

The usual adult dosage is:

 | Single Doses (Range) | Maximum 24-Hour Dose
Codeine Phosphate | 15 mg to 60 mg | 360 mg
Acetaminophen | 300 mg to 1000 mg | 4000 mg

Doses may be repeated up to every 4 hours.

The prescriber must determine the number of tablets per dose, and the maximum number of tablets per 24 hours based upon the above dosage guidance. This information should be conveyed in the prescription.

It should be kept in mind, however, that tolerance to codeine can develop with continued use and that the incidence of untoward effects is dose related. Adult doses of codeine higher than 60 mg fail to give commensurate relief of pain but merely prolong analgesia and are associated with an appreciably increased incidence of undesirable side effects. Equivalently high doses in children would have similar effects.

HOW SUPPLIED

Repackaged by Aphena Pharma Solutions - TN.
See Repackaging Information for available configurations.

Each Acetaminophen and Codeine Phosphate Tablet USP 300 mg/15 mg tablet contains acetaminophen 300 mg and codeine phosphate 15 mg. It is available as a round, white to off-white tablet debossed with “2” on one side and an M on the other side.

Bottles of 100......................................... NDC 0406-0483-01

Each Acetaminophen and Codeine Phosphate Tablet USP 300 mg/30 mg tablet contains acetaminophen 300 mg and codeine phosphate 30 mg. It is available as a round, white to off-white tablet debossed with “3” on one side and an M on the other side.

Bottles of 20........................................... NDC 0406-0484-20
Bottles of 30........................................... NDC 0406-0484-03
Bottles of 50........................................... NDC 0406-0484-50
Bottles of 100......................................... NDC 0406-0484-01
Bottles of 1000....................................... NDC 0406-0484-10
Unit Dose (10 x 10)............................... NDC 0406-0484-62

Each Acetaminophen and Codeine Phosphate Tablet USP 300 mg/60 mg tablet contains acetaminophen 300 mg and codeine phosphate 60 mg. It is available as a round, white to off-white tablet debossed with “4” on one side and an M on the other side.

Bottles of 100......................................... NDC 0406-0485-01
Bottles of 500......................................... NDC 0406-0485-05

Store at 20° to 25°C (68° to 77°F) [see USP Controlled Room Temperature].

Dispense in tight, light-resistant container as defined in the USP.

Mallinckrodt, the “M” brand mark, the Mallinckrodt Pharmaceuticals logo and M are trademarks of a Mallinckrodt company.

© 2013 Mallinckrodt.

Mallinckrodt Inc.
Hazelwood, MO 63042 USA

Rev 10/2013

Mallinckrodt™
Pharmaceuticals

Repackaging Information

Please reference the How Supplied section listed above for a description of individual tablets or capsules. This drug product has been received by Aphena Pharma - TN in a manufacturer or distributor packaged configuration and repackaged in full compliance with all applicable cGMP regulations. The package configurations available from Aphena are listed below:

Count | 15/300mg | 30/300mg | 60/300mg
9000 | - | 67544-002-09 | -
15 | - | 67544-002-15 | -
20 | - | 67544-002-20 | -
30 | - | 67544-002-30 | -
40 | - | 67544-002-40 | -
45 | - | 67544-002-45 | -
50 | - | 67544-002-50 | -
56 | - | 67544-002-46 | -
60 | - | 67544-002-53 | 67544-003-53
75 | - | 67544-002-55 | -
84 | - | 67544-002-54 | -
90 | 67544-001-60 | 67544-002-60 | 67544-003-60
60 | - | 67544-002-53 | 67544-003-53
112 | - | 67544-002-72 | -
150 | - | 67544-002-75 | -
180 | - | 67544-002-80 | 67544-003-80
200 | - | 67544-002-85 | -
240 | - | 67544-002-90 | 67544-003-90
300 | - | 67544-002-93 | -

Store between 20°-25°C (68°-77°F). See USP Controlled Room Temperature. Dispense in a tight light-resistant container as defined by USP. Keep this and all drugs out of the reach of children.

Repackaged by:
Cookeville, TN 38506
20140505SC

PRINCIPAL DISPLAY PANEL - 15/300mg

NDC 67544-001 - Codeine Phosphate/APAP 15/300mg - Rx Only

PRINCIPAL DISPLAY PANEL - 30/300mg

NDC 67544-002 - Codeine Phosphate/APAP 30/300mg - Rx Only

PRINCIPAL DISPLAY PANEL - 60/300mg

NDC 67544-003 - Codeine Phosphate/APAP 60/300mg - Rx Only